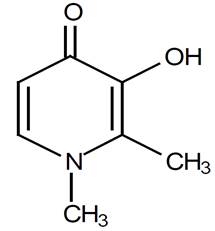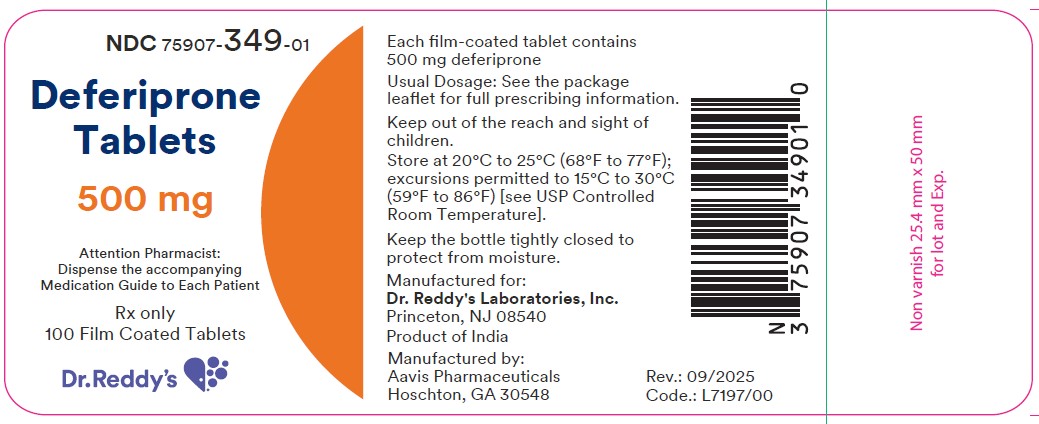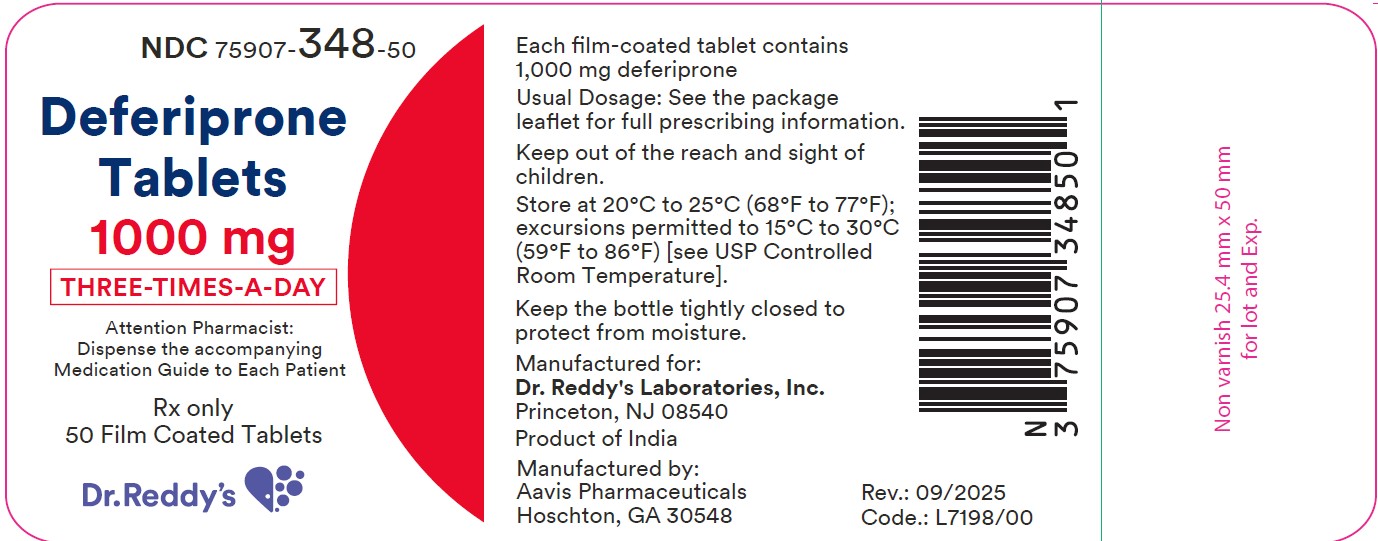 DRUG LABEL: DEFERIPRONE
NDC: 75907-348 | Form: TABLET, COATED
Manufacturer: DR. REDDY'S LABORATORIES, INC.
Category: prescription | Type: HUMAN PRESCRIPTION DRUG LABEL
Date: 20251215

ACTIVE INGREDIENTS: DEFERIPRONE 1000 mg/1 1
INACTIVE INGREDIENTS: METHYLCELLULOSE (15 CPS); CROSPOVIDONE; MAGNESIUM STEARATE; HYPROMELLOSE 2910 (6 MPA.S); TITANIUM DIOXIDE; POLYETHYLENE GLYCOL 400

HIGHLIGHTS OF PRESCRIBING INFORMATION

These highlights do not include all the information needed to use DEFERIPRONE TABLETS safely and effectively. See full prescribing information for DEFERIPRONE TABLETS.
DEFERIPRONE tablets, for oral use
Initial U.S. Approval: 2011

WARNING

WARNING: AGRANULOCYTOSIS AND NEUTROPENIA

See full prescribing information for complete boxed warning.

- Deferiprone tablets can cause agranulocytosis that can lead to serious infections and death. Neutropenia may precede the development of agranulocytosis. (5.1)
- Measure the absolute neutrophil count (ANC) before starting deferiprone tablets and monitor regularly while on therapy. (5.1)
- Interrupt deferiprone tablets therapy if neutropenia develops. (5.1)
- Interrupt deferiprone tablets if infection develops and monitor the ANC more frequently. (5.1)
- Advise patients taking deferiprone tablets to report immediately any symptoms indicative of infection. (5.1)

RECENT MAJOR CHANGES

Warnings and Precautions, Agranulocytosis and Neutropenia (5.1) 03/2025

1 INDICATIONS AND USAGE

Deferiprone tablets are an iron chelator indicated for the treatment of transfusional iron overload in adult patients with thalassemia syndromes when current chelation therapy is inadequate. (1)

Limitations of Use

Safety and effectiveness have not been established for the treatment of transfusional iron overload in patients with myelodysplastic syndrome or in patients with Diamond Blackfan anemia.

2 DOSAGE AND ADMINISTRATION

- Deferiprone Tablets are available in two formulations. A 1,000 mg formulation and a 500 mg formulation, which have different dosing regimens to achieve the same total daily dosage. (2.1)
- To prevent medication errors, before prescribing and dispensing, ensure that the tablet formulation is appropriate for the dosing regimen. Each tablet has distinct identifying characteristics. (2.1,3)
- Deferiprone Tablets (three times a day), 1,000 mg:
  - Starting oral dosage: 75 mg/kg/day (actual body weight) in three divided doses (2.3)
  - Maximum oral dosage: 99 mg/kg/day (actual body weight) in three divided doses (2.3)
- Deferiprone Tablets (three times a day), 500 mg:
  - Starting oral dosage: 75 mg/kg/day (actual body weight) in three divided doses (2.4)
  - Maximum oral dosage: 99 mg/kg/day (actual body weight) in three divided doses (2.4)

3 DOSAGE FORMS AND STRENGTHS

- Tablets (three times a day): 1,000 mg with functional scoring (3)
- Tablets (three times a day): 500 mg with functional scoring (3)

4 CONTRAINDICATIONS

Hypersensitivity to deferiprone or to any of the excipients in the formulations. (4)

5 WARNINGS AND PRECAUTIONS

- Liver Enzyme Elevations: Monitor monthly and discontinue for persistent elevations. (5.2)
- Zinc Deficiency: Monitor during therapy and supplement for deficiency. (5.3)
- Embryo-Fetal Toxicity: Can cause fetal harm. (5.4)

6 ADVERSE REACTIONS

- The most common adverse reactions in patients with thalassemia (incidence ≥ 6%) are nausea, vomiting, abdominal pain, arthralgia, ALT increased and neutropenia. (6)

To report SUSPECTED ADVERSE REACTIONS, contact Dr. Reddy's Laboratories, Inc. at 1-888-375-3784 or FDA at 1-800-FDA-1088 or www.fda.gov/medwatch

7 DRUG INTERACTIONS

- Drugs Associated with Neutropenia or Agranulocytosis: Avoid co- administration. If co-administration is unavoidable, closely monitor the absolute neutrophil count. (7.1)
- UGT1A6 Inhibitors: Avoid co-administration. (7.2)
- Polyvalent Cations: Allow at least a 4-hour interval between administration of Deferiprone Tablets and drugs or supplements containing polyvalent cations (e.g., iron, aluminum, or zinc). (2, 7.2)

8 USE IN SPECIFIC POPULATIONS

Lactation: Advise not to breastfeed. (8.2)

Pediatric use information is approved for Chiesi USA, Inc.'s FERRIPROX® (deferiprone) tablets. However, due to Chiesi USA, Inc.'s marketing exclusivity rights, this drug product is not labeled with that information.

FULL PRESCRIBING INFORMATION

WARNING

AGRANULOCYTOSIS AND NEUTROPENIA

- Deferiprone tablets can cause agranulocytosis that can lead to serious infections and death. Neutropenia may precede the development of agranulocytosis. [see Warnings and Precautions (5.1)]
- Measure the absolute neutrophil count (ANC) before starting deferiprone tablets therapy and monitor regularly while on therapy.
- Interrupt deferiprone tablets therapy if neutropenia develops. [see Warnings and Precautions (5.1)]
- Interrupt deferiprone tablets if infection develops, and monitor the ANC more frequently. [see Warnings and Precautions (5.1)]
- Advise patients taking deferiprone tablets to report immediately any symptoms indicative of infection. [see Warnings and Precautions (5.1)]

1 INDICATIONS AND USAGE

Deferiprone tablets are indicated for the treatment of transfusional iron overload in adult patients with thalassemia syndromes when current chelation therapy is inadequate.

Limitations of Use

- Safety and effectiveness have not been established for the treatment of transfusional iron overload in patients with myelodysplastic syndrome or in patients with Diamond Blackfan anemia.

Pediatric use information is approved for Chiesi USA, Inc.'s FERRIPROX® (deferiprone) tablets. However, due to Chiesi USA, Inc.'s marketing exclusivity rights, this drug product is not labeled with that information.

2 DOSAGE AND ADMINISTRATION

2.1 Important Dosage and Administration Information

Deferiprone Tablets are available in a 1,000 mg formulation and a 500 mg formulation, which have different oral dosing regimens to achieve the same total daily dosage.

- DeferiproneTablets (three times a day) - 1,000 mg - given three times a day [see Dosage and Administration (2.3)]
- DeferiproneTablets - 500 mg - given three times a day [see Dosage and Administration (2.4)]

To prevent medication errors, before prescribing and dispensing, ensure that the tablet formulation is appropriate for the dosing regimen. Each tablet has distinct identifying characteristics [see Dosage Forms and Strengths (3)].

Monitoring for Safety

Due to the risk of agranulocytosis, monitor ANC before and during deferiprone tablets therapy.

Test ANC prior to start of deferiprone tablets therapy and monitor on the following schedule during treatment:

- First six months of therapy: Monitor ANC weekly;
- Next six months of therapy: Monitor ANC once every two weeks;
- After one year of therapy: Monitor ANC every two to four weeks (or at the patient's blood transfusion interval in patients that have not experienced an interruption due to any decrease in ANC [see Warnings and Precautions (5.1)].

Due to the risk of hepatic transaminase elevations, monitor ALT before and monthly during deferiprone tablets therapy [see Warnings and Precautions (5.2)].

Due to the risk of zinc deficiency, monitor zinc levels before and regularly during deferiprone tablets therapy [see Warnings and Precautions (5.3)].

2.3 Recommended Dosage for 1,000 mg Deferiprone Tablets (three times a day) for Adult Patients with Transfusional Iron Overload due to Thalassemia Syndromes

Starting Dosage for Three Times a Day Tablets

The recommended starting oral dosage of deferiprone tablets (three times a day) is 75 mg/kg/day (actual body weight), in three divided doses per day. Table 3 describes the number of deferiprone tablets (three times a day) needed to achieve the 75 mg/kg/day total starting dosage). Round dose to the nearest 500 mg (half-tablet).

Table 3: Number of Deferiprone 1,000 mg Tablets (three times a day) Needed to Achieve the Total Starting Daily Dosage of 75 mg/kg (rounded to the nearest half-tablet)
Body Weight (kg) | Morning | Midday | Evening
20 | 0.5 | 0.5 | 0.5
30 | 1 | 0.5 | 1
40 | 1 | 1 | 1
50 | 1.5 | 1 | 1.5
60 | 1.5 | 1.5 | 1.5
70 | 2 | 1.5 | 2
80 | 2 | 2 | 2
90 | 2.5 | 2 | 2.5

To minimize gastrointestinal upset when first starting therapy, dosing can start at 45 mg/kg/day and increase weekly by 15 mg/kg/day increments until the full prescribed dose is achieved.

Dosage Adjustments for Three Times Daily Tablets

Tailor dosage adjustments for deferiprone tablets (three times a day) to the individual patient's response and therapeutic goals (maintenance or reduction of body iron burden). The maximum oral dosage is 99 mg/kg/day (actual body weight), in three divided doses per day. Table 4 describes the number of deferiprone tablets (three times a day) needed to achieve the 99 mg/day total maximum daily dosage.

Table 4: Number of Deferiprone 1,000 mg Tablets (three times a day) Needed to Achieve the Maximum Total Daily Dosage of 99 mg/kg (rounded to the nearest half-tablet)
Body Weight (kg) | Morning | Midday | Evening
20 | 0.5 | 0.5 | 1
30 | 1 | 1 | 1
40 | 1.5 | 1 | 1.5
50 | 1.5 | 1.5 | 2
60 | 2 | 2 | 2
70 | 2.5 | 2 | 2.5
80 | 2.5 | 2.5 | 3
90 | 3 | 3 | 3

Pediatric use information is approved for Chiesi USA, Inc.'s FERRIPROX® (deferiprone) tablets. However, due to Chiesi USA, Inc.'s marketing exclusivity rights, this drug product is not labeled with that information.

2.4 Recommended Dosage for 500 mg Deferiprone Tablets (three times a day) for Adult Patients with Transfusional Iron Overload due to Thalassemia Syndromes

Starting Dosage for Three Times a Day Tablets

The recommended starting oral dosage of deferiprone tablets (three times a day) is 75 mg/kg/day (actual body weight), in three divided doses per day. Table 5 describes the number of deferiprone tablets (three times a day) needed to achieve the 75 mg/kg/day total starting dosage. Round dose to the nearest 250 mg (half-tablet).

Table 5: Number of Deferiprone 500 mg Tablets (three times a day) Needed to Achieve the Total Starting Daily Dosage of 75 mg/kg dose (rounded to the nearest half-tablet)
Body Weight (kg) | Morning | Midday | Evening
20 | 1 | 1 | 1
30 | 1.5 | 1.5 | 1.5
40 | 2 | 2 | 2
50 | 2.5 | 2.5 | 2.5
60 | 3 | 3 | 3
70 | 3.5 | 3.5 | 3.5
80 | 4 | 4 | 4
90 | 4.5 | 4.5 | 4.5

To minimize gastrointestinal upset when first starting therapy, dosing can start at 45 mg/kg/day and increase weekly by 15 mg/kg/day increments until the full prescribed dose is achieved.

Dosage Adjustments

Tailor dosage adjustments for deferiprone tablets (three times a day) to the individual patient's response and therapeutic goals (maintenance or reduction of body iron burden). The maximum oral dosage is 99 mg/kg/day (actual body weight), in three divided doses per day. Table 6 describes the number of deferiprone tablets (three times a day) needed to achieve the 99 mg/day total maximum daily dosage.

Table 6: Number of Deferiprone 500 mg Tablets (three times a day) Needed to Achieve the Maximum Total Daily Dosage of 99 mg/kg dose (rounded to the nearest half-tablet)
Body Weight (kg) | Morning | Midday | Evening
20 | 1.5 | 1 | 1.5
30 | 2 | 2 | 2
40 | 3 | 2 | 3
50 | 3.5 | 3 | 3.5
60 | 4 | 4 | 4
70 | 5 | 4.5 | 4.5
80 | 5.5 | 5 | 5.5
90 | 6 | 6 | 6

Pediatric use information is approved for Chiesi USA, Inc.'s FERRIPROX® (deferiprone) tablets. However, due to Chiesi USA, Inc.'s marketing exclusivity rights, this drug product is not labeled with that information.

2.5 Monitoring Ferritin Levels to Assess Efficacy

Monitor serum ferritin concentration every two to three months to assess the effect of deferiprone tablets on body iron stores. If the serum ferritin is consistently below 500 mcg/L, consider temporarily interrupting deferiprone tablets therapy until serum ferritin rises above 500 mcg/L.

2.6 Dosage Modification for Drug Interactions

Allow at least a 4-hour interval between administration of deferiprone tablets and other drugs or supplements containing polyvalent cations such as iron, aluminum, or zinc [see Drug Interactions (7.2), Clinical Pharmacology (12.3)].

3 DOSAGE FORMS AND STRENGTHS

- Tablets (three times a day): 1,000 mg with functional scoring are "white to off-white, capsule shaped film coated scored tablets, with debossed bisect separating "A" and "67'' on one side and plain on other side".
- Tablets: 500 mg with functional scoring are "white to off-white, capsule shaped film coated scored tablets, with debossed bisect separating "A" and "66" on one side and plain on other side".

4 CONTRAINDICATIONS

Deferiprone tablets are contraindicated in patients with known hypersensitivity to deferiprone or to any of the excipients in the formulations. The following reactions have been reported in association with the administration of deferiprone: Henoch-Schönlein purpura; urticaria; and periorbital edema with skin rash [see Adverse Reactions (6.2)].

5 WARNINGS AND PRECAUTIONS

5.1 Agranulocytosis and Neutropenia

Fatal agranulocytosis can occur with deferiprone tablets use. Deferiprone tablets can also cause neutropenia, which may foreshadow agranulocytosis. Measure the absolute neutrophil count (ANC) before starting deferiprone tablets therapy and monitor it regularly while on therapy [see Dosage and Administration (2.1)].

Reduction in the frequency of ANC monitoring should be considered on an individual patient basis, according to the health care provider's assessment of the patient's understanding of the risk minimization measures required during therapy.

Interrupt deferiprone tablets therapy if neutropenia develops (ANC < 1.5 x 10^9/L).

Interrupt deferiprone tablets if infection develops and monitor the ANC frequently.

Advise patients taking deferiprone tablets to immediately interrupt therapy and report to their physician if they experience any symptoms indicative of infection.

The incidence of agranulocytosis was 1% of patients in pooled clinical trials of 642 patients with thalassemia syndromes. The mechanism of deferiprone-associated agranulocytosis is unknown. Agranulocytosis and neutropenia usually resolve upon discontinuation of deferiprone tablets, but there have been reports of agranulocytosis leading to death.

Implement a plan to monitor for and to manage agranulocytosis and neutropenia prior to initiating deferiprone tablets treatment.

For agranulocytosis (ANC <0.2 x 10^9/L) and severe neutropenia (0.2 x 10^9/L ≤ ANC < 0.5 x 10^9/L):

Consider hospitalization and other management as clinically appropriate.

Do not resume deferiprone tablets in patients who have developed agranulocytosis unless potential benefits outweigh potential risks. Do not rechallenge patients who have developed neutropenia with deferiprone tablets unless potential benefits outweigh potential risks.

For neutropenia (ANC < 1.5 x 10^9/L and ≥ 0.5 x 10^9/L):

Instruct the patient to immediately discontinue deferiprone tablets and all other medications with a potential to cause neutropenia.

Obtain a complete blood cell (CBC) count, including a white blood cell (WBC) count corrected for the presence of nucleated red blood cells, an absolute neutrophil count (ANC), and a platelet count daily until recovery (ANC ≥ 1.5 x 10^9/L).

5.2 Liver Enzyme Elevations

In pooled clinical trials, 7.5% of 642 patients with thalassemia syndromes treated with deferiprone tablets developed increased ALT values. Four (0.62%) deferiprone tablets -treated subjects discontinued the drug due to increased serum ALT levels and 1 (0.16%) due to an increase in both ALT and AST.

Monitor serum ALT values monthly during therapy with deferiprone tablets and consider interruption of therapy if there is a persistent increase in the serum transaminase levels [see Dosage and Administration (2.1)].

5.3 Zinc Deficiency

Decreased plasma zinc concentrations have been observed on deferiprone tablets therapy. Monitor plasma zinc annually, and supplement in the event of a deficiency [see Dosage and Administration (2.1)].

5.4 Embryo-Fetal Toxicity

Based on findings from animal reproduction studies and evidence of genotoxicity, deferiprone tablets can cause fetal harm when administered to a pregnant woman. The available data on the use of deferiprone tablets in pregnant women are insufficient to inform risk. In animal studies, administration of deferiprone during the period of organogenesis resulted in embryo-fetal death and malformations at doses lower than equivalent human clinical doses. Advise pregnant women and females of reproductive potential of the potential risk to the fetus [see Use in Specific Populations (8.1)].

Advise females of reproductive potential to use an effective method of contraception during treatment with deferiprone tablets and for at least six months after the last dose. Advise males with female partners of reproductive potential to use effective contraception during treatment with deferiprone tablets and for at least three months after the last dose [see Use in Specific Populations (8.1, 8.3)].

6 ADVERSE REACTIONS

The following clinically significant adverse reactions are described below and elsewhere in the labeling:

- Agranulocytosis and Neutropenia [see Warnings and Precautions (5.1)]
- Liver Enzyme Elevations [see Warnings and Precautions (5.2)]
- Zinc Deficiency [see Warnings and Precautions (5.3)]

6.1 Clinical Trial Experience

Because clinical trials are conducted under widely varying conditions, adverse reaction rates observed in the clinical trials of a drug cannot be directly compared to rates in the clinical trials of another drug and may not reflect the rates observed in practice.

The following adverse reaction information represents the pooled data collected from single arm or active-controlled clinical trials with deferiprone tablets (three times a day).

Thalassemia Syndromes

The safety of deferiprone tablets was evaluated in the pooled clinical trial database [see Clinical Studies (14.1)]. Patients received deferiprone tablets (three times a day). Deferiprone tablets were administered orally three times a day (total daily dose either 50, 75, or 99 mg/kg), N=642. Among 642 patients receiving deferiprone tablets, 492 (76.6%) were exposed for 6 months or longer and 365 (56.9%) were exposed for greater than one year.

The median age of patients who received deferiprone tablets was 19 years (range 1, 77 years); 50.2% female; 71.2% White, 17.8% Asian, 9.2% Unknown, 1.2% Multi-racial and 0.6% Black.

The most serious adverse reaction reported in clinical trials with deferiprone tablets was agranulocytosis [see Warnings and Precautions (5.1)].

The most common adverse reactions (≥6%) reported during clinical trials were nausea, vomiting, abdominal pain, arthralgia, alanine aminotransferase increased and neutropenia.

The table below lists the adverse drug reactions that occurred in at least 1% of patients treated with deferiprone tablets in clinical trials in patients with thalassemia syndromes.

Table 7: Adverse reactions occurring in ≥ 1% of deferiprone tablets -treated patients with thalassemia syndromes
Body System | (N=642)
Adverse Reaction | % Patients
BLOOD AND LYMPHATIC SYSTEM
DISORDERS
Neutropenia [Neutropenia includes events of severe neutropenia (ANC ≥0.2 x 10^9/L and <0.5 x 10^9/L).] | 7
Agranulocytosis [Agranulocytosis (ANC< 0.2 x 10^9/L)] | 1
GASTROINTESTINAL DISORDERS
Nausea | 13
Abdominal pain/discomfort | 10
Vomiting | 10
Diarrhea | 3
Dyspepsia | 2
INVESTIGATIONS
Alanine aminotransferase increased | 7
Weight increased | 2
Aspartate aminotransferase increased | 1
METABOLISM AND NUTRITION
DISORDERS
Increased appetite | 4
Decreased appetite | 1
MUSCULOSKELETAL AND
CONNECTIVE TISSUE DISORDERS
Arthralgia | 10
Back pain | 2
Pain in extremity | 2
Arthropathy | 1
NERVOUS SYSTEM DISORDERS
Headache | 2

Gastrointestinal symptoms such as nausea, vomiting, and abdominal pain were the most frequent adverse reactions reported by patients participating in clinical trials and led to the discontinuation of deferiprone tablets therapy in 1.6% of patients.

Chromaturia (reddish/brown discoloration of the urine) is a result of the excretion of iron in the urine.

6.2 Postmarketing Experience

The following additional adverse reactions have been reported in patients receiving deferiprone tablets. Because these reactions are reported voluntarily from a population of uncertain size, it is not always possible to reliably estimate their frequency or to establish a causal relationship to drug exposure.

Blood and lymphatic system disorders: thrombocytosis, pancytopenia.

Cardiac disorders: atrial fibrillation, cardiac failure.

Congenital, familial and genetic disorders: hypospadias.

Eye disorders: diplopia, papilledema, retinal toxicity.

Gastrointestinal disorders: enterocolitis, rectal hemorrhage, gastric ulcer, pancreatitis, parotid gland enlargement.

General disorders and administration site conditions: chills, edema peripheral, multi-organ failure.

Hepatobiliary disorders: jaundice, hepatomegaly.

Immune system disorders: anaphylactic shock, hypersensitivity.

Infections and infestations: cryptococcal cutaneous infection, enteroviral encephalitis, pharyngitis, pneumonia, sepsis, furuncle, infectious hepatitis, rash pustular, subcutaneous abscess.

Investigations: blood bilirubin increased, blood creatinine phosphokinase increased.

Metabolism and nutrition disorders: metabolic acidosis, dehydration.

Musculoskeletal and connective tissue disorders: myositis, chondropathy, trismus.

Nervous system disorders: cerebellar syndrome, cerebral hemorrhage, convulsion, gait disturbance, intracranial pressure increased, psychomotor skills impaired, pyramidal tract syndrome, somnolence.

Psychiatric disorders: bruxism, depression, obsessive-compulsive disorder.

Renal disorders: glycosuria, hemoglobinuria.

Respiratory, thoracic and mediastinal disorders: acute respiratory distress syndrome, epistaxis, hemoptysis, pulmonary embolism.

Skin, subcutaneous tissue disorders: hyperhidrosis, periorbital edema, photosensitivity reaction, pruritis, urticaria, rash, Henoch- Schönlein purpura.

Vascular disorders: hypotension, hypertension.

7 DRUG INTERACTIONS

7.1 Drugs Associated with Neutropenia or Agranulocytosis

Avoid co-administration of deferiprone tablets with other drugs known to be associated with neutropenia or agranulocytosis. If co-administration is unavoidable, closely monitor the absolute neutrophil count [see Warnings and Precautions (5.1)].

7.2 Effect of Other Drugs on deferiprone tablets

UDP-Glucuronosyltransferases (UGT)

Avoid use of UGT1A6 inhibitors (e.g., diclofenac, probenecid, or silymarin (milk thistle)) with deferiprone tablets [see Dosage and Administration (2), Adverse Reactions (6.1), Clinical Pharmacology (12.3)].

Polyvalent Cations

Deferiprone has the potential to bind polyvalent cations (e.g., iron, aluminum, and zinc); allow at least a 4-hour interval between deferiprone tablets and other medications (e.g., antacids), or supplements containing these polyvalent cations [see Dosage and Administration (2)].

8 USE IN SPECIFIC POPULATIONS

8.1 Pregnancy

Risk Summary

In animal reproduction studies, oral administration of deferiprone to pregnant rats and rabbits during organogenesis at doses 33% and 49%, respectively, of the maximum recommended human dose (MRHD) resulted in structural abnormalities, embryo-fetal mortality and alterations to growth (see Data). The limited available data from deferiprone use in pregnant women are insufficient to inform a drug-associated risk of major birth defects and miscarriage. Based on evidence and developmental toxicity in animal studies, deferiprone tablets can cause fetal harm when administered to a pregnant woman. Advise pregnant women and females of reproductive potential of the potential risk to a fetus.

The estimated background risk of major birth defects and miscarriage for the indicated population is unknown. All pregnancies have a background risk of birth defect, loss, or other adverse outcomes. In the U.S. general population, the estimated background risk of major birth defects and of miscarriage is 2-4% and 15-20%, respectively.

Data

Human Data

Post-marketing data available from 39 pregnancies of deferiprone-treated patients and 10 pregnancies of partners of deferiprone treated patients are as follows:

Of the 39 pregnancies in deferiprone-treated patients, 23 resulted in healthy newborns, 6 ended in spontaneous abortion, 9 had unknown outcomes, and 1 infant was born with anal atresia, nephroptosis, ventricular septal defect, hemivertebra and urethral fistula.

Of the 10 pregnancies in partners of deferiprone-treated patients, 5 resulted in healthy newborns, 1 resulted in a healthy newborn with slight hypospadias, 1 was electively terminated, 1 resulted in the intrauterine death of twins, and 2 had unknown outcomes.

Animal Data

During organogenesis, pregnant rats and rabbits received deferiprone at oral doses of 0, 30, 80 or 200 mg/kg/day, and 0, 10, 50, or 150 mg/kg/day, respectively. The daily dose was administered as two equal divided doses approximately 7 hours apart. Doses of 200 mg/kg/day in rats and 150 mg/kg/day in rabbits, approximately 33% and 49% of the MRHD, respectively, resulted in increased post-implantation loss and reduced fetal weights in the presence of maternal toxicity (reduced maternal body weight and body weight gain in both rats and rabbits; abnormal large placenta at low incidence in rats). The 200 mg/kg/day dose in rats resulted in external, visceral and skeletal fetal malformations such as cranial malformations, cleft palate, limb malrotation, anal atresia, internal hydrocephaly, anophthalmia and fused bones. The dose of 150 mg/kg/day in rabbits resulted in external fetal malformations (partially opened eyes) and minor blood vessel and skeletal variations.

In rats, malformations including micrognathia and persistent ductus arteriosus could be observed in the absence of maternal toxicity at doses equal to or greater than 30 and 80 mg/kg/day, approximately 5% and 13% of the MHRD, respectively.

8.2 Lactation

Risk Summary

There is no information regarding the presence of deferiprone in human milk, the effects on the breastfed child, or the effects on milk production.

Because of the potential for serious adverse reactions in the breastfed child, including the potential for tumorigenicity shown for deferiprone in animal studies, advise patients that breastfeeding is not recommended during treatment with deferiprone tablets, and for at least 2 weeks after the last dose.

8.3 Females and Males of Reproductive Potential

Pregnancy Testing

Pregnancy testing is recommended for females of reproductive potential prior to initiating deferiprone tablets.

Contraception

Females

Deferiprone tablets can cause embryo-fetal harm when administered to a pregnant woman [see Use in Specific Populations (8.1)]. Advise female patients of reproductive potential to use effective contraception during treatment with deferiprone tablets and for at least 6 months after the last dose.

Males

Based on genotoxicity findings, advise males with female partners of reproductive potential to use effective contraception during treatment with deferiprone tablets and for at least 3 months after the last dose [see Nonclinical Toxicology (13.1)].

8.4 Pediatric Use

Safety and effectiveness of deferiprone tablets have not been established in pediatric patients with chronic iron overload due to blood transfusions who are less than 8 years of age.

Pediatric use information is approved for Chiesi USA, Inc.'s FERRIPROX® (deferiprone) tablets. However, due to Chiesi USA, Inc.'s marketing exclusivity rights, this drug product is not labeled with that information.

8.5 Geriatric Use

Clinical studies of deferiprone did not include sufficient numbers of subjects aged 65 and over to determine whether they respond differently from younger subjects. Other reported clinical experience has not identified differences in responses between the elderly and younger patients.

10 OVERDOSAGE

No cases of acute overdose have been reported. There is no specific antidote to deferiprone tablets overdose.

Neurological disorders such as cerebellar symptoms, diplopia, lateral nystagmus, psychomotor slowdown, hand movements and axial hypotonia have been observed in children treated with 2.5 to 3 times the recommended dose for more than one year. The neurological disorders progressively regressed after deferiprone discontinuation.

11 DESCRIPTION

Deferiprone tablets contain 1,000 mg or 500 mg deferiprone (3-hydroxy-1,2-dimethylpyridin-4-one), a synthetic, orally active, iron-chelating agent. The molecular formula for deferiprone is C7H9NO2 and its molecular weight is 139.15 g/mol. Deferiprone has the following structural formula:

Deferiprone is a white to pinkish-white powder. It is sparingly soluble in deionized water (14.3 mg/mL) and has a melting point range of 272°C - 278°C.

Deferiprone Tablets (three times a day), 1,000 mg

White to off-white, capsule shaped film coated scored tablets, with debossed bisect separating "A" and "67'' on one side and plain on other side. The tablets can be broken in half along the score line. Each tablet contains 1,000 mg deferiprone and the following inactive ingredients: Tablet core - methylcellulose, crospovidone, and magnesium stearate; Coating - hypromellose, macrogol, and titanium dioxide.

Deferiprone Tablets, 500 mg

White to off-white, capsule shaped film coated scored tablets, with debossed bisect separating "A" and "66" on one side and plain on other side. The tablets can be broken in half along the score line. Each tablet contains 500 mg deferiprone and the following inactive ingredients: Tablet core - methylcellulose, crospovidone and magnesium stearate; Coating - hypromellose, macrogol and titanium dioxide.

12 CLINICAL PHARMACOLOGY

12.1 Mechanism of Action

Deferiprone is a chelating agent with an affinity for ferric ions (iron III). Deferiprone binds with ferric ions to form neutral 3:1 (deferiprone:iron) complexes that are stable at physiological pH.

12.2 Pharmacodynamics

No clinical studies were performed to assess the relationship between the dose of deferiprone and the amount of iron eliminated from the body.

Cardiac Electrophysiology

At the maximum approved recommended dose, deferiprone does not prolong the QT interval to any clinically relevant extent.

12.3 Pharmacokinetics

Deferiprone Tablets (three times a day), 1,000 mg and 500 mg

The mean Cmax and AUC of deferiprone was 20 mcg/mL and 50 mcg.h/mL, respectively, in healthy subjects. The dose proportionality of deferiprone over the approved recommended dosage range is unknown.

Absorption

Deferiprone appeared in the blood within 5 to 10 minutes after oral administration. Peak serum concentration of deferiprone was reached approximately 1 to 2 hours after a single dose.

Effect of Food

No clinically significant differences in the pharmacokinetics of deferiprone were observed following administration with food.

Elimination

The elimination half-life of deferiprone is approximately 2 hours.

Metabolism

Deferiprone is metabolized primarily by UGT1A6. The major metabolite of deferiprone is the 3-O-glucuronide, which lacks iron binding capability.

Excretion

Following oral administration, 75% to 90% of the administered dose was recovered in urine (primarily as metabolite) in the first 24 hours.

Specific Populations

No clinically significant differences in the pharmacokinetics of deferiprone were observed based on sex, race/ethnicity, body weight, mild to severe (eGFR 15 to 89 mL/min/1.73 m^2) renal impairment, or mild (Child Pugh Class A) to moderate (Child Pugh Class B) hepatic impairment. The effect of age, including geriatric or pediatric populations, end stage renal disease or severe (Child Pugh Class C) hepatic impairment on the pharmacokinetics of deferiprone is unknown.

Drug Interaction Studies

In Vitro Studies

UGTIA6 Inhibitors: Phenylbutazone (UGT1A6 inhibitor) decreased glucuronidation of deferiprone by up to 78%.

Polyvalent Cations: Deferiprone has the potential to bind polyvalent cations (e.g., iron, aluminum, and zinc).

13 NONCLINICAL TOXICOLOGY

13.1 Carcinogenesis, Mutagenesis, Impairment of Fertility

Carcinogenicity studies have not been conducted with deferiprone. However, in view of the genotoxicity results, and the findings of mammary gland hyperplasia and mammary gland tumors in rats treated with deferiprone in the 52-week toxicology study, tumor formation in carcinogenicity studies must be regarded as likely.

Deferiprone was positive in a mouse lymphoma cell assay in vitro. Deferiprone was clastogenic in an in vitro chromosomal aberration test in mice and in a chromosomal aberration test in Chinese Hamster Ovary cells. Deferiprone given orally or intraperitoneally was clastogenic in a bone marrow micronucleus assay in non-iron-loaded mice. A micronucleus test was also positive when mice predosed with iron dextran were treated with deferiprone. Deferiprone was not mutagenic in the Ames bacterial reverse mutation test.

A fertility and early embryonic development study of deferiprone was conducted in rats. Sperm counts, motility and morphology were unaffected by treatment with deferiprone. There were no effects observed on male or female fertility or reproductive function at the highest dose which was 25% of the MRHD.

14 CLINICAL STUDIES

The following information is based on studies with Deferiprone Tablets (three times a day).

14.1 Transfusional Iron Overload in Patients with Thalassemia Syndromes

In a prospective, planned, pooled analysis of patients with thalassemia syndromes from several studies, the efficacy of deferiprone was assessed in transfusion-dependent iron overload patients in whom previous iron chelation therapy had failed or was considered inadequate due to poor tolerance. The main criterion for chelation failure was serum ferritin > 2,500 mcg/L before treatment with deferiprone. Deferiprone therapy (35-99 mg/kg/day) was considered successful in individual patients who experienced a ≥ 20% decline in serum ferritin within one year of starting therapy.

Data from a total of 236 patients were analyzed. Of the 224 patients with thalassemia who received deferiprone monotherapy and were eligible for serum ferritin analysis, 105 (47%) were male and 119 (53%) were female. The mean age of these patients was 18.2 years (range 2 to 62; 91 patients were <17).

For the patients in the analysis, the endpoint of at least a 20% reduction in serum ferritin was met in 50% (of 236 subjects), with a 95% confidence interval of 43% to 57%.

A small number of patients with thalassemia and iron overload were assessed by measuring the change in the number of milliseconds (ms) in the cardiac MRI T2* value before and after treatment with deferiprone for one year. There was an increase in cardiac MRI T2* from a mean at baseline of 11.8 ± 4.9 ms to a mean of 15.1 ± 7.0 ms after approximately one year of treatment. The clinical significance of this observation is not known.

16 HOW SUPPLIED/STORAGE AND HANDLING

Deferiprone Tablets (three times a day), 1,000 mg with functional scoring

Deferiprone Tablets (three times a day) are white to off-white, capsule shaped film coated scored tablets, with debossed bisect separating "A" and "67'' on one side and plain on other side. They are provided in HDPE bottles.

1,000 mg film-coated tablets, 50 tablets NDC 75907-348-50

Store at 20°C to 25°C (68°F to 77°F); excursions permitted to 15°C to 30°C (59°F to 86°F) [see USP Controlled Room Temperature].

Keep the bottle tightly closed to protect from moisture.

Deferiprone Tablets, 500 mg with functional scoring

Deferiprone Tablets are white to off-white, capsule shaped film coated scored tablets, with debossed bisect separating "A" and "66" on one side and plain on other side. They are provided in HDPE bottles.

500 mg film-coated tablets, 100 tablets NDC 75907-349-01

Store at 20°C to 25°C (68°F to 77°F); excursions permitted to 15°C to 30°C (59°F to 86°F) [see USP Controlled Room Temperature].

Keep the bottle tightly closed to protect from moisture.

17 PATIENT COUNSELING INFORMATION

Advise the patient to read the FDA-approved patient labeling (Medication Guide)

- Instruct patients and their caregivers to store Deferiprone tablets at 68°F to 77°F (20°C to 25°C); excursions permitted to 59°F to 86°F (15°C to 30°C) [see USP Controlled Room Temperature].
- Deferiprone Tablets (three times a day), 1,000 mg:

Store in the originally supplied bottle, closed tightly to protect from moisture.

Advise patients to take the first dose of Deferiprone tablets in the morning, the second dose at midday, and the third dose in the evening. Clinical experience suggests that taking deferiprone tablets with meals may reduce nausea.

- Deferiprone Tablets, 500 mg:

Store in the originally supplied bottle, closed tightly to protect from moisture.

Advise patients to take the first dose of deferiprone tablets in the morning, the second dose at midday, and the third dose in the evening. Clinical experience suggests that taking Deferiprone tablets with meals may reduce nausea.

- If a dose of this medicine has been missed, take it as soon as possible. However, if it is almost time for the next dose, skip the missed dose and go back to the regular dosing schedule. Do not catch-up or double doses.
- Inform patients of the risks of developing agranulocytosis and the need for regular blood testing before and during their treatment to monitor for decreases in their ANC. Instruct them to immediately interrupt therapy and report to their physician if they experience any symptoms of infection such as fever, sore throat or flu-like symptoms [see Dosage and Administration (2.1) and Warnings and Precautions (5.1)] in order to check their ANC within 24 hours. Advise them if they are unable to reach their physician, seek care from another provider so as not to delay medical care.
- Inform patients of the risk of abnormal liver transaminases and the need for regular blood testing before and during their treatment to monitor for increases in ALT [see Dosage and Administration (2.1) and Warnings and Precautions (5.2)].
- Inform patients of the risk of zinc deficiency and the need for regular blood testing before and during their treatment to monitor for reductions in zinc [see Dosage and Administration (2.1) and Warnings and Precautions (5.3)].
- Advise patients to contact their physician in the event of overdose.
- Inform patients that their urine might show a reddish/brown discoloration due to the excretion of the iron-deferiprone complex. This is a very common sign of the desired effect, and it is not harmful.

Embryo-Fetal toxicity

Advise pregnant women and females of reproductive potential of the potential risk to a fetus. Advise females to inform their healthcare provider of a known or suspected pregnancy [see Warnings and Precautions (5.4) and Use in Specific Populations (8.1)]. Advise female patients of reproductive potential to use effective contraception during treatment with deferiprone tablets and for at least six months after the last dose [see Use in Specific Populations (8.1,8.3)]. Advise males with female partners of reproductive potential to use effective contraception during treatment with deferiprone tablets and for at least three months after the last dose [see Use in Specific Populations (8.3) and Nonclinical Toxicology (13.1)].

Lactation

Advise females not to breastfeed during treatment with deferiprone tablets and for at least 2 weeks after the last dose [see Use in Specific Populations (8.2)].

Manufactured by:

Aavis Pharmaceuticals Inc.

Hoschton, GA 30548 U.S.A.

Manufactured for:

Dr. Reddy's Laboratories, Inc.

Princeton, NJ 08540

Product of India

Revised: 11/2025

Code: L7199/02

SPL MEDGUIDE

Medication Guide
Deferiprone (de fer' i prone) Tablets

What is the most important information I should know about deferiprone tablets?
Deferiprone tablets can cause serious side effects , including a very low white blood cell count. One type of white blood cell that is important for fighting infections is called a neutrophil. If your neutrophil count is low (neutropenia), you may be at risk of developing a serious infection that can lead to death. Neutropenia is common with Deferiprone Tablets and can become severe in some people. Severe neutropenia is known as agranulocytosis. If you develop agranulocytosis, you will be at risk of developing serious infections that can lead to death.
Your healthcare provider will do a blood test before you start Deferiprone tablets and regularly during treatment to check your neutrophil count. If you develop neutropenia, your healthcare provider should check your blood counts every day until your white blood cell count improves. Your healthcare provider may temporarily stop treatment with Deferiprone tablets if you develop neutropenia or infection.
Stop taking Deferiprone tablets and call your healthcare provider or get medical help right away if you develop any of these symptoms of infection:

- fever
- sore throat or mouth sores
- flu-like symptoms
- chills and severe shaking

It is important for you to have your white blood cell count checked within 24 hours of developing symptoms of an infection to see if you have severe neutropenia (agranulocytosis). Do not delay getting medical care if you are unable to reach your healthcare provider.
See "What are the possible side effects of Deferiprone tablets?" for more information about side effects.

What are deferiprone tablets?
Deferiprone tablets are a prescription medicine used to treat iron overload from blood transfusions in adults with thalassemia syndromes when current iron removal (chelation) therapy does not work well enough.
It is not known if deferiprone tablets are safe and effective to treat iron overload due to blood transfusions:

- in people with myelodysplastic syndrome or Diamond Blackfan anemia
- in children less than 8 years of age

Do not take deferiprone tablets if you are allergic to deferiprone or any of the ingredients in deferiprone tablets.
See the end of this Medication Guide for a complete list of ingredients in deferiprone tablets.

Before taking deferiprone tablets, tell your healthcare provider about all of your medical conditions, including if you:

- have liver problems
- are pregnant or plan to become pregnant. Deferiprone tablets can harm your unborn baby. You should avoid becoming pregnant during treatment with deferiprone tablets. Tell your healthcare provider right away if you become pregnant or think you may be pregnant during treatment with deferiprone tablets.

Females who are able to become pregnant:

- Your healthcare provider should do a pregnancy test before you start treatment with deferiprone tablets.
- You should use effective birth control during treatment with deferiprone tablets and for at least 6 months after the last dose.

Males with female partners who are able to become pregnant:

- You should use effective birth control during treatment with deferiprone tablets and for at least 3 months after the last dose.

- are breastfeeding or plan to breastfeed. It is not known if deferiprone tablets passes into your breast milk. Do not breastfeed during treatment with deferiprone tablets and for at least 2 weeks after the last dose.

Tell your healthcare provider about all the medicines you take, including prescription and over-the-counter medicines, vitamins and herbal supplements.

How should I take deferiprone tablets?

- Take deferiprone tablets exactly as your healthcare provider tells you.
- Your healthcare provider will prescribe deferiprone tablets based on your body weight.
- Your healthcare provider will check your body iron level during treatment with deferiprone tablets and may change your dose if needed. Your healthcare provider may also change your dose of deferiprone tablets if you have certain side effects. Do not change your dose of deferiprone tablets unless your healthcare provider tells you to.
- There are 2 types of deferiprone tablets. Be sure you are taking the correct tablet and ask your healthcare provider if unsure.

Deferiprone tablets
1000 mg
3 times each day
Take your first dose in the morning, the second dose at mid-day, and the third dose in the evening

Deferiprone tablets
500 mg
3 times each day
Take your first dose in the morning, the second dose at mid-day, and the third dose in the evening.

- Taking deferiprone tablets with meals may help reduce nausea.
- If you must take a medicine to treat indigestion (antacid), or supplements that contain iron, aluminum, or zinc during treatment with deferiprone tablets, al ow at least 4 hours between taking deferiprone tablets and these products.
- If you take too many deferiprone tablets, call your healthcare provider.

If you miss a dose, take it as soon as you remember. If it is almost time for your next dose, skip the missed dose and then continue with your regular schedule. Do not try to catch-up or take 2 doses at the same time to make up for a missed dose.

What are the possible side effects of deferiprone tablets?
Deferiprone Tablets can cause serious side effects, including:

- See "What is the most important information I should know about deferiprone tablets?"
- Increased liver enzyme levels in your blood. Your healthcare provider should do blood tests to check your liver function before you start and then monthly during treatment with deferiprone tablets. Your healthcare provider may temporarily stop treatment with deferiprone tablets if you develop increased liver enzyme levels and they continue to be increased.
- Decreased levels of zinc in your blood. Your healthcare provider will do blood tests to check your zinc levels before you start and during treatment with deferiprone tablets, and may prescribe a zinc supplement for you if your zinc levels are low.

The most common side effects of deferiprone tablets in people with thalassemia include:

- nausea
- vomiting
- stomach-area (abdominal) pain
- joint pain
- abnormal liver function tests
- low white blood cells

Deferiprone Tablets may cause a change in urine color to reddish-brown. This is not harmful and is expected during treatment with Deferiprone Tablets.
These are not all of the possible side effects of deferiprone tablets.
Call your doctor for medical advice about side effects. You may report side effects to FDA at 1-800-FDA-1088.

How should I store deferiprone tablets?

Deferiprone Tablets 1,000 mg
3 times each day
Store at room temperature between 68°F to 77°F (20°C to 25°C).
Store deferiprone tablets in the original bottle and tightly closed to protect from moisture.

Deferiprone Tablets 500 mg
3 times each day
Store at room temperature between 68°F to 77°F (20°C to 25°C).

Keep deferiprone tablets and all medicines out of the reach of children.

General information about the safe and effective use of deferiprone tablets.
Medicines are sometimes prescribed for purposes other than those listed in a Medication Guide. Do not use deferiprone tablets for a condition for which it was not prescribed. Do not give deferiprone tablets to other people, even if they have the same symptoms that you have. It may harm them. You can ask your pharmacist or healthcare provider for information about deferiprone tablets that is written for health professionals.

What are the ingredients in deferiprone tablets?

Deferiprone Tablets 1,000 mg
(3 times each day)

Deferiprone Tablets 500 mg
(3 times each day)

Active ingredient: deferiprone
Inactive ingredients: Tablet core methylcellulose, crospovidone, and magnesium stearate
Coating - hypromellose, macrogol, and titanium dioxide.

Active ingredient: deferiprone
Inactive ingredients: Tablet core methylcellulose, crospovidone, and magnesium stearate
Coating - hypromellose, macrogol, and titanium dioxide.

Manufactured by:
Aavis Pharmaceuticals Inc.
Hoschton, GA 30548 U.S.A.
Manufactured for:
Dr. Reddy's Laboratories, Inc.
Princeton, NJ 08540
Product of India
Revised: 09/2025
Code: L7200/00

This Medication Guide has been approved by the U.S. Food and Drug Administration

Pediatric use information is approved for Chiesi USA, Inc.'s FERRIPROX® (deferiprone) tablets. However, due to Chiesi USA, Inc.'s marketing exclusivity rights, this drug product is not labeled with that information.

PACKAGE LABEL.PRINCIPAL DISPLAY PANEL

NDC 75907-349-01

Deferiprone Tablets

500 mg

Attention Pharmacist: Dispense the accompanying Medication Guide to Each Patient

Rx only

100 Film Coated Tablets

Dr. Reddy's

NDC 75907-348-50

Deferiprone Tablets

1000 mg

Attention Pharmacist: Dispense the accompanying Medication Guide to Each Patient

Rx only

50 Film Coated Tablets

Dr. Reddy's